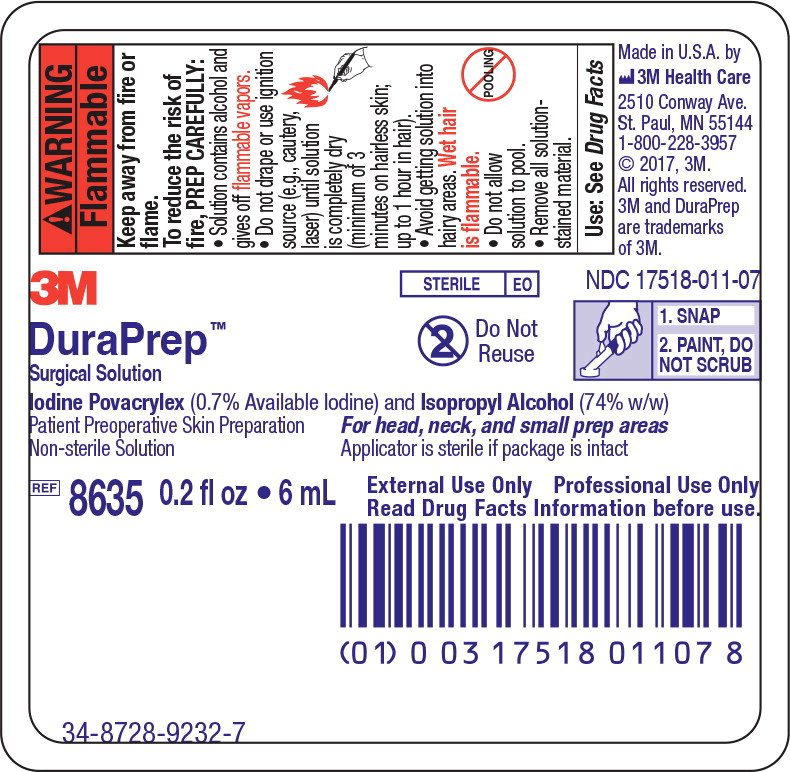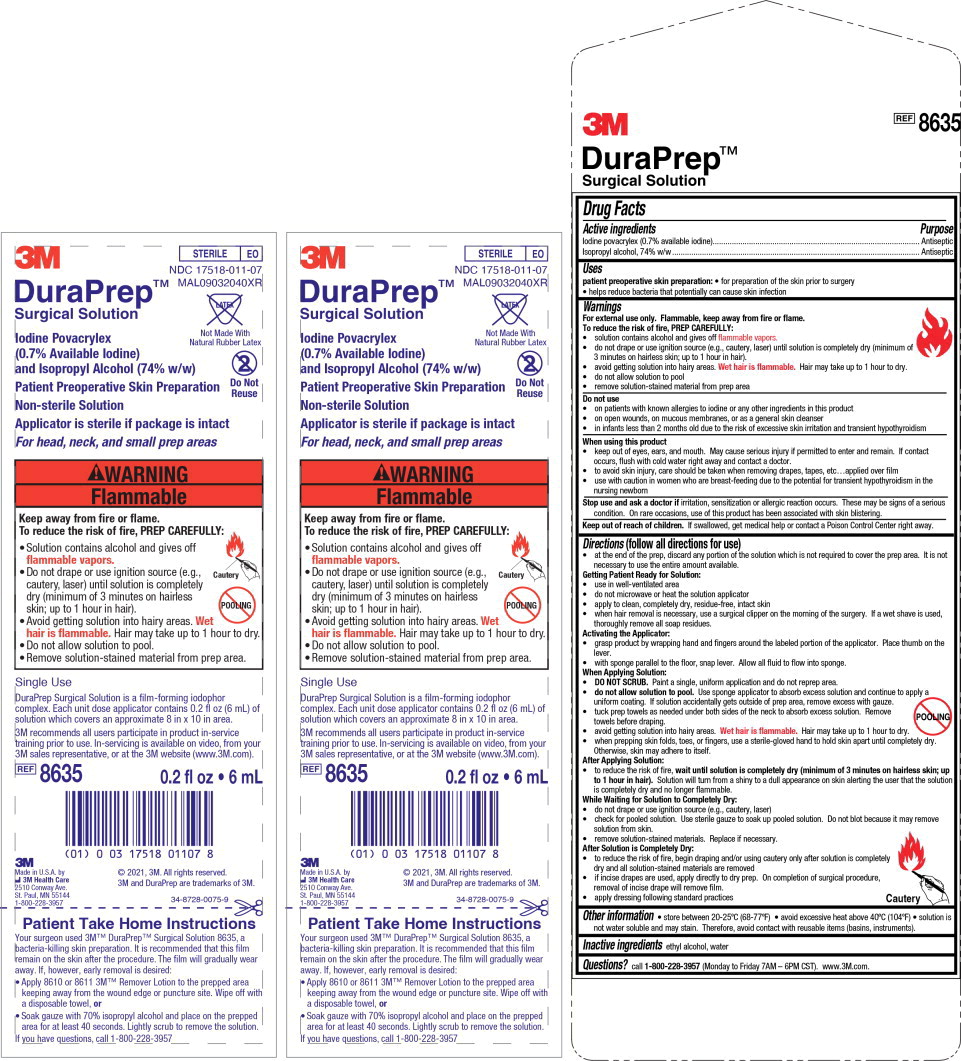 DRUG LABEL: 3M DuraPrep Surgical
NDC: 17518-011 | Form: SOLUTION
Manufacturer: Solventum US LLC
Category: otc | Type: HUMAN OTC DRUG LABEL
Date: 20250214

ACTIVE INGREDIENTS: Iodine Povacrylex 6.02 mg/1 mL; Isopropyl Alcohol 636.4 mg/1 mL
INACTIVE INGREDIENTS: Alcohol; Water

Active ingredients

Iodine povacrylex (0.7% available iodine)

Isopropyl alcohol, 74% w/w

Purpose

Antiseptic

Antiseptic

Uses

patient preoperative skin preparation:

- for preparation of the skin prior to surgery
- helps reduce bacteria that potentially can cause skin infection

Warnings

For external use only. Flammable, keep away from fire or flame.

To reduce the risk of fire, PREP CAREFULLY:

- solution contains alcohol and gives off flammable vapors
- do not drape or use ignition source (e.g., cautery, laser) until solution is completely dry (minimum of 3 minutes on hairless skin; up to 1 hour in hair).
- avoid getting solution into hairy areas. Wet hair is flammable. Hair may take up to 1 hour to dry.
- do not allow solution to pool
- remove solution-stained material from prep area

Do not use

- on patients with known allergies to iodine or any other ingredients in this product
- on open wounds, on mucous membranes, or as a general skin cleanser
- in infants less than 2 months old due to the risk of excessive skin irritation and transient hypothyroidism

When using this product

- keep out of eyes, ears, and mouth. May cause serious injury if permitted to enter and remain. If contact occurs, flush with cold water right away and contact a doctor.
- to avoid skin injury, care should be taken when removing drapes, tapes, etc…applied over film
- use with caution in women who are breast-feeding due to the potential for transient hypothyroidism in the nursing newborn

Stop use and ask a doctor if irritation, sensitization or allergic reaction occurs. These may be signs of a serious condition. On rare occasions, use of this product has been associated with skin blistering.

Keep out of reach of children. If swallowed, get medical help or contact a Poison Control Center right away.

Directions (follow all directions for use)

- at the end of the prep, discard any portion of the solution which is not required to cover the prep area. It is not necessary to use the entire amount available.

Getting Patient Ready for Solution:

- use in well-ventilated area
- do not microwave or heat the solution applicator
- apply to clean, completely dry, residue-free, intact skin
- when hair removal is necessary, use a surgical clipper on the morning of the surgery. If a wet shave is used, thoroughly remove all soap residues.

Activating the Applicator:

- grasp product by wrapping hand and fingers around the labeled portion of the applicator. Place thumb on the lever.
- with sponge face parallel to the floor, snap lever. Allow all fluid to flow into sponge.

When Applying Solution:

- DO NOT SCRUB. Paint a single, uniform application and do not reprep area.
- do not allow solution to pool. Use sponge applicator to absorb excess solution and continue to apply a uniform coating. If solution accidentally gets outside of prep area, remove excess with gauze.
- tuck prep towels as needed under both sides of the neck to absorb excess solution. Remove towels before draping.
- avoid getting solution into hairy areas. Wet hair is flammable. Hair may take up to 1 hour to dry.
- when prepping skin folds, toes, or fingers, use a sterile-gloved hand to hold skin apart until completely dry. Otherwise, skin may adhere to itself.

After Applying Solution:

- to reduce the risk of fire, wait until solution is completely dry (minimum of 3 minutes on hairless skin; up to 1 hour in hair). Solution will turn from a shiny to a dull appearance on skin alerting the user that the solution is completely dry and no longer flammable.

While Waiting for Solution to Completely Dry:

- do not drape or use ignition source (e.g., cautery, laser)
- check for pooled solution. Use sterile gauze to soak up pooled solution. Do not blot because it may remove solution from skin.
- remove solution-stained materials. Replace if necessary.

After Solution is Completely Dry:

- to reduce the risk of fire, begin draping and/or using cautery only after solution is completely dry and all solution-stained materials are removed
- if incise drapes are used, apply directly to dry prep. On completion of surgical procedure, removal of incise drape will remove film.
- apply dressing following standard practices

Other information

- store between 20-25ºC (68-77ºF)
- avoid excessive heat above 40ºC (104ºF)
- solution is not water soluble and may stain. Therefore, avoid contact with reusable items (basins, instruments).

Inactive ingredients

ethyl alcohol, water

Questions?

call 1-800-228-3957 (Monday to Friday 7AM – 6PM CST). www.3M.com.

Principle Display Panel – 6 mL Applicator Label

3M

STERILE EO

NDC 17518-011-07

Do Not Reuse

1. SNAP

2. PAINT, DO

NOT SCRUB

DuraPrep TM

Surgical Solution

Iodine Povacrylex (0.7% Available Iodine) and Isopropyl Alcohol (74% w/w)

Patient Preoperative Skin Preparation For head, neck, and small prep areas

Non-sterile Solution Applicator is sterile if package is intact

REF 8635 0.2 fl oz • 6 mL

External Use Only Professional Use Only

Read Drug Facts Information before use.

Made in U.S.A. by 3M Health Care

2510 Conway Ave., St. Paul, MN 55144

1-800-228-3957 © 2017, 3M. All rights reserved.

3M and Duraprep are trademarks of 3M.

Principal Display Panel – 6 mL Insert Label

3M

STERILE EO

NDC 17518-011-07

MAL09032040XR

DuraPrep TM

Surgical Solution

Iodine Povacrylex (0.7% Available Iodine)

and Isopropyl Alcohol (74% w/w)

Patient Preoperative Skin Preparation

Non-sterile Solution

Applicator is sterile if package is intact

For head, neck, and small prep areas

Latex-Free

Not Made With Natural Latex

Do Not Reuse

Single Use

DuraPrep Surgical Solution is a film-forming iodophor complex. Each unit dose

applicator contains 0.2 fl oz (6 mL) of solution which covers an approximate 8

in x 10 in area.

3M recommends all users participate in product in-service training prior to use.

In-servicing is available on video, from your 3M sales representative, or at the

3M website (www.3M.com).

REF 8635 0.2 fl oz • 6 mL

3M

Made in U.S.A. by

3M Health Care

2510 Conway Ave

St. Paul, MN 55144

1-800-228-3957

© 2021, 3M. All rights reserved.

3M and DuraPrep are trademarks of 3M